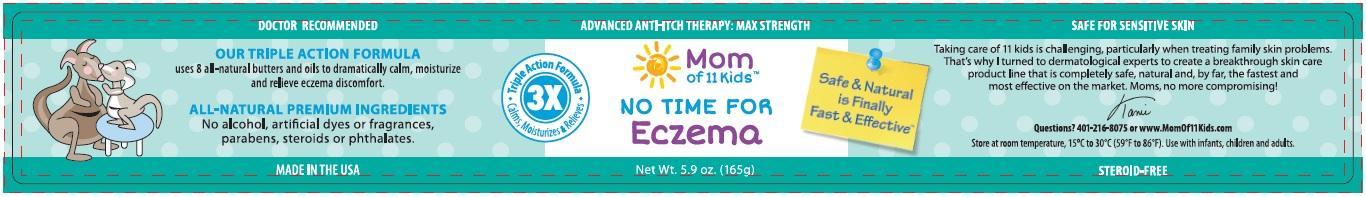 DRUG LABEL: Mom of 11 Kids No Time For Eczema
NDC: 24909-506 | Form: OINTMENT
Manufacturer: Aidance Skincare & Topical Solutions, LLC
Category: homeopathic | Type: HUMAN OTC DRUG LABEL
Date: 20150820

ACTIVE INGREDIENTS: THUJA OCCIDENTALIS LEAF 3 [hp_X]/100 g; COMFREY 1 [hp_X]/100 g
INACTIVE INGREDIENTS: ARGAN OIL; CHAMOMILE FLOWER OIL; COCONUT OIL; COTTONSEED OIL; JOJOBA OIL; GARCINIA INDICA FRUIT; MAGNESIUM OXIDE; MANGIFERA INDICA SEED BUTTER; SHEA BUTTER; SILVER OXIDE; WHITE WAX; ZINC OXIDE

Drug Facts

Active Ingredients

Thuja Occidentalis 3X HPUS, Comfrey 1X HPUS

Purpose

Thuja Occidentalis - Eczematic/dry skin relief
Comfrey - Inflammatory relief

Uses

Temporarily relieves minor skin irritation and itching due to rashes, eczema.

Warnings

For external use only. Stop use and ask a doctor if condition worsens or if symptoms persist for more than 7 days, or clear up and occur again within a few days. When using this product avoid contact with eyes.

Keep out of reach of children.

If swallowed, get medical help or contact a Poison Control Center right away.

Directions

Apply a thin layer to irritated skin at first signs of eczema symptoms. Repeat up to 3 times daily for best results.

Inactive Ingredients

Argan Oil, Beeswax (organic), Chamomile Oil, Coconut Oil, Cotton Seed Oil, Jojoba Seed Oil (golden), Kokum Butter, Magnesium Oxide, Mango Butter, Shea Butter, Silver Oxide, Zinc Oxide.

PRINCIPAL DISPLAY PANEL - 165g Label

Mom of 11 Kids™
NO TIME FOR™
Eczema
Max Strength
Safe & Natural is Finally Fast & Effective™
Net Wt. 5.9 oz. (165g)